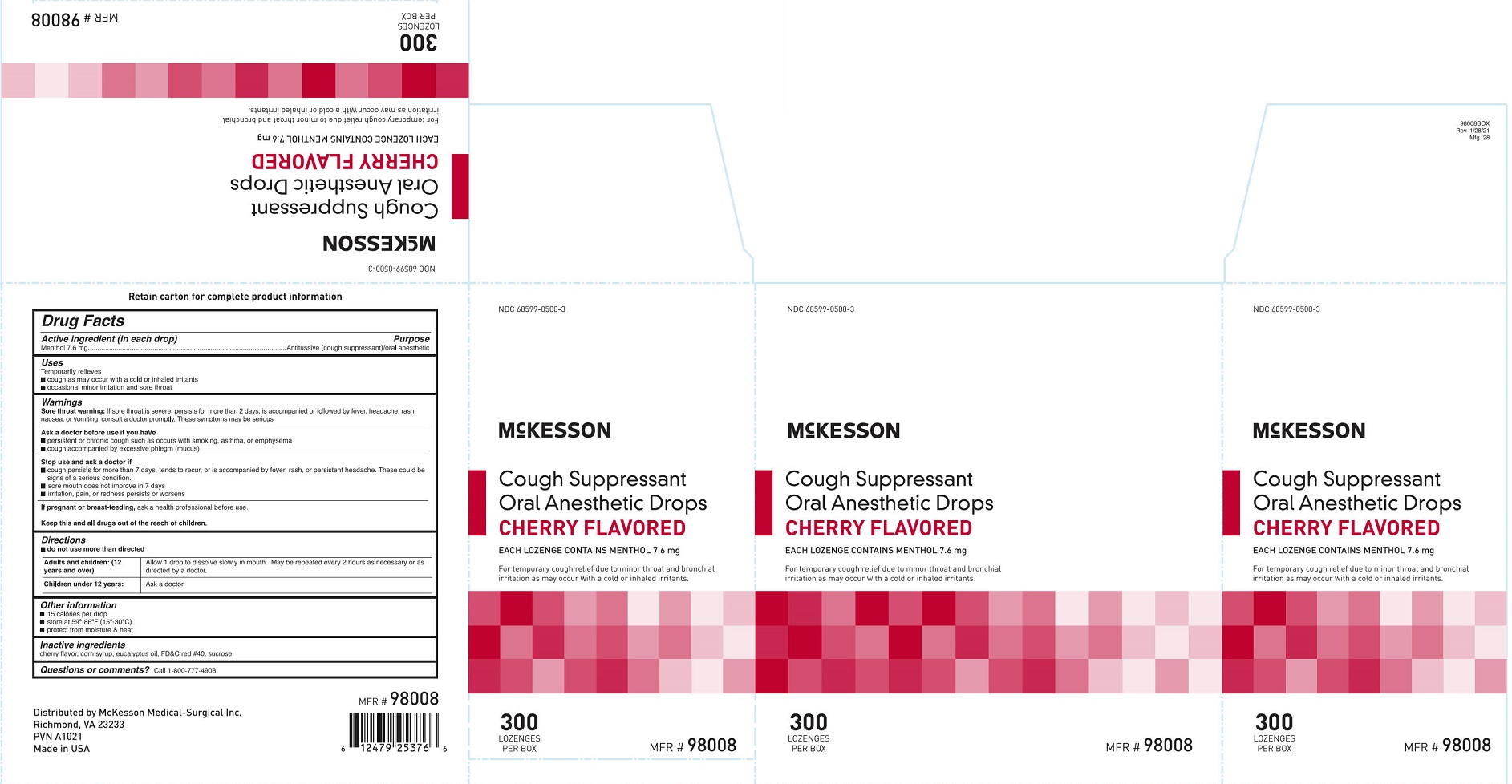 DRUG LABEL: McKesson Cough Supressant
NDC: 68599-0500 | Form: LOZENGE
Manufacturer: McKesson Medical-Surgical
Category: otc | Type: HUMAN OTC DRUG LABEL
Date: 20250909

ACTIVE INGREDIENTS: MENTHOL 7.6 mg/1 1
INACTIVE INGREDIENTS: EUCALYPTUS OIL; FD&C RED NO. 40; SUCROSE; CORN SYRUP

Mckesson Cough Supressant Cherry Flavored

Drug Facts

Active ingredients

Menthol 7.6 mg

Purpose

Antitussive (cough supressant)/oral anesthetic

Uses

Temporarily relieves

■ cough as may occur with a cold or inhaled irritants

■ occasional minor irritation and sore throat

Warnings

Sore throat warning:

If sore throat is severe, persists for more than 2 days, is accompanied or followed by fever, headache, rash, nausea, or vomiting, consult a doctor promptly. These symptoms may be serious.

Ask a doctor before use if you have

- persistent or chronic cough such as occurs with smoking, asthma, or emphysema
- cough accompanied by excessive phlegm (mucus)

Stop use and ask a doctor if

- cough persists for more than 1 week, tends to recur, or is accompanied by fever, rash, or persistent

headache. These could be signs of a serious condition.

- sore mouth does not improve in 7 days
- irritation, pain, or redness persists or worsens

PREGNANCY OR BREAST FEEDING

If pregnant or breast-feeding, ask a health professional before use.

KEEP OUT OF REACH OF CHILDREN

Keep this and all drugs out of the reach of children.

Directions

- do not use more than directed

Adults and children:
(12 years and over)

Allow 1 drop to dissolve slowly in the mouth. May be repeated every 2 hours as necessary or as directed by a doctor.

Children under 12 years:

Ask a doctor

Other information

- 15 calories per drop
- store at 59-86°F (15°-30°C)
- protect from moisture & heat

Inactive ingredients

cherry flavor, corn syrup, eucalyptus oil, FD&C red #40, sucrose

Questions or comments? Call 1-800-777-4908

PACKAGE LABEL

NDC 68599-0500-3

McKesson

Cough Suppressant

Oral Anesthetic Drops

Cherry Flavored

Each Lozenge Contains Menthol 7.6 mg

For temporary cough relief due to minor throat and bronchial irritation as may occur with a cold or inhaled irritants.

300

Lozenges Per Box

MFR # 98008